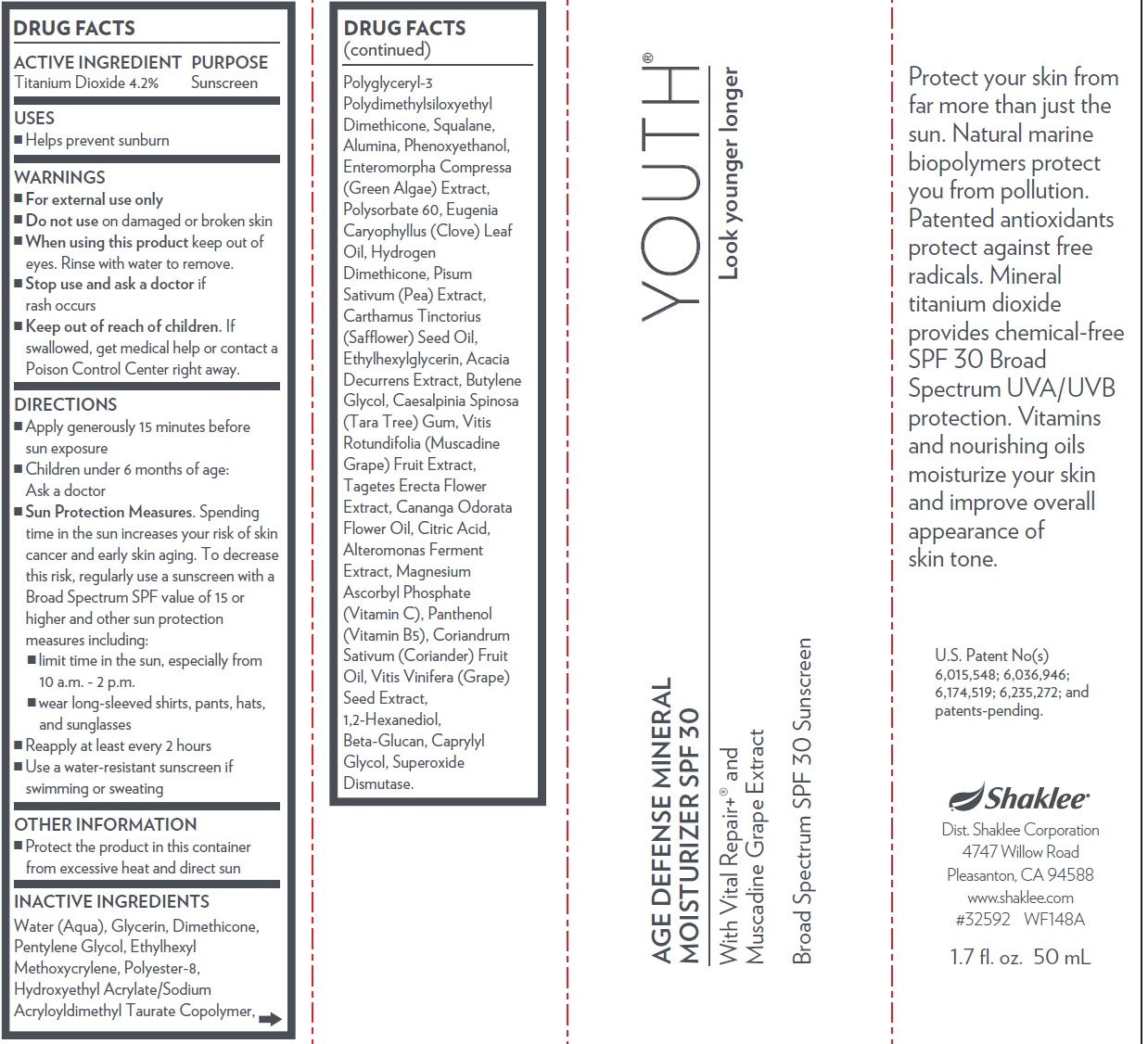 DRUG LABEL: Shaklee Youth Age Defense Mineral Moisturizer SPF 30
NDC: 59899-023 | Form: CREAM
Manufacturer: Shaklee Corporation
Category: otc | Type: HUMAN OTC DRUG LABEL
Date: 20231109

ACTIVE INGREDIENTS: TITANIUM DIOXIDE 42 mg/1 mL
INACTIVE INGREDIENTS: WATER; GLYCERIN; DIMETHICONE; PENTYLENE GLYCOL; ETHYLHEXYL METHOXYCRYLENE; SQUALANE; ALUMINUM OXIDE; PHENOXYETHANOL; POLYSORBATE 60; CLOVE LEAF OIL; PEA; SAFFLOWER OIL; ETHYLHEXYLGLYCERIN; BUTYLENE GLYCOL; CAESALPINIA SPINOSA RESIN; MUSCADINE GRAPE; TAGETES ERECTA FLOWER; YLANG-YLANG OIL; CITRIC ACID MONOHYDRATE; MAGNESIUM ASCORBYL PHOSPHATE; PANTHENOL; CORIANDER OIL; VITIS VINIFERA SEED; 1,2-HEXANEDIOL; CAPRYLYL GLYCOL; SUPEROXIDE DISMUTASE (SACCHAROMYCES CEREVISIAE)

Shaklee Youth Age Defense Mineral Moisturizer SPF 30

ACTIVE INGREDIENT

Titanium Dioxide 4.2%

PURPOSE

Sunscreen

USES

- Helps prevent sunburn

WARNINGS

- For external use only

Do not use

- on damaged or broken skin

When using this product

- keep out of eyes. Rinse with water to remove.

Stop use and ask a doctor

- if rash occurs

Keep out of reach of children.

- If swallowed, get medical help or contact a Poison Control Center right away.

DIRECTIONS

- Apply generously 15 minutes before sun exposure
- Children under 6 months of age: Ask a doctor
- Spending time in the sun increases your risk of skin cancer and early skin aging. To decrease this risk, regularly use a sunscreen with a Broad Spectrum SPF value of 15 or higher and other sun protection measures including: Sun Protection Measures.
- limit time in the sun, especially from 10 a.m. - 2 p.m.
- wear long-sleeved shirts, pants, hats, and sunglasses
- Reapply at least every 2 hours
- Use a water-resistant sunscreen if swimming or sweating

OTHER INFORMATION

Protect the product in this container from excessive heat and direct sun

INACTIVE INGREDIENTS

Water (Aqua), Glycerin, Dimethicone, Pentylene Glycol, Ethylhexyl Methoxycrylene, Polyester-8, Hydroxyethyl Acrylate/Sodium Acryloyldimethyl Taurate Copolymer, Polyglyceryl-3 Polydimethylsiloxyethyl Dimethicone, Squalane, Alumina, Phenoxyethanol, Enteromorpha Compressa (Green Algae) Extract, Polysorbate 60, Eugenia Caryophyllus (Clove) Leaf Oil, Hydrogen Dimethicone, Pisum Sativum (Pea) Extract, Carthamus Tinctorius (Saflower) Seed Oil, Ethylhexylglycerin, Acacia Decurrens Extract, Butylene Glycol, Caesalpinia Spinosa (Tara Tree) Gum, Vitis Rotundifolia (Muscadine Grape) Fruit Extract, Tagetes Erecta Flower Extract, Cananga Odorata Flower Oil, Citric Acid, Alteromonas Ferment Extract, Magnesium Ascorbyl Phosphate (Vitamin C), Panthenol (Vitamin B5), Coriandrum Sativum (Coriander) Fruit Oil, Vitis Vinifera (Grape) Seed Extract, 1,2-Hexanediol, Beta-Glucan, Caprylyl Glycol, Superoxide Dismutase.